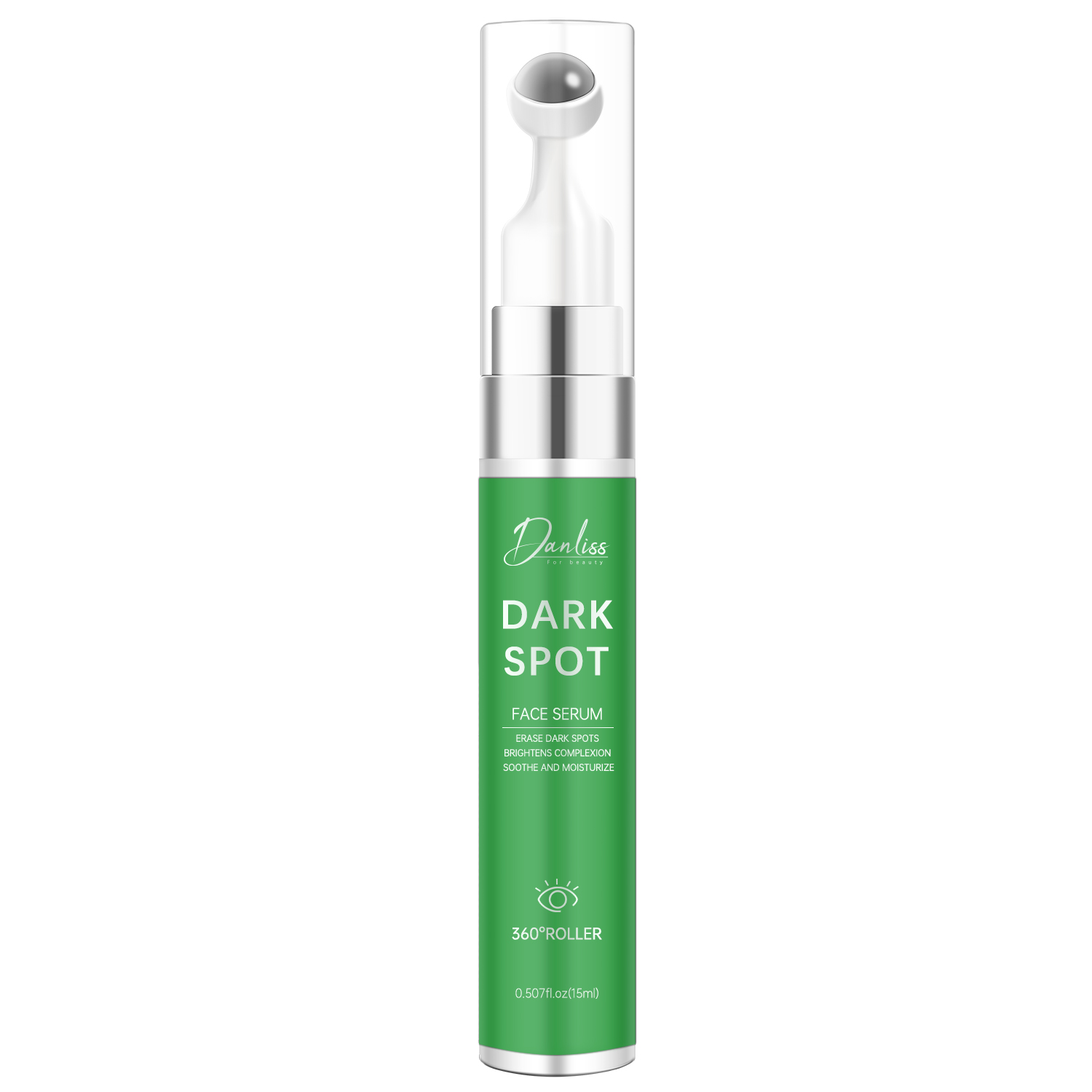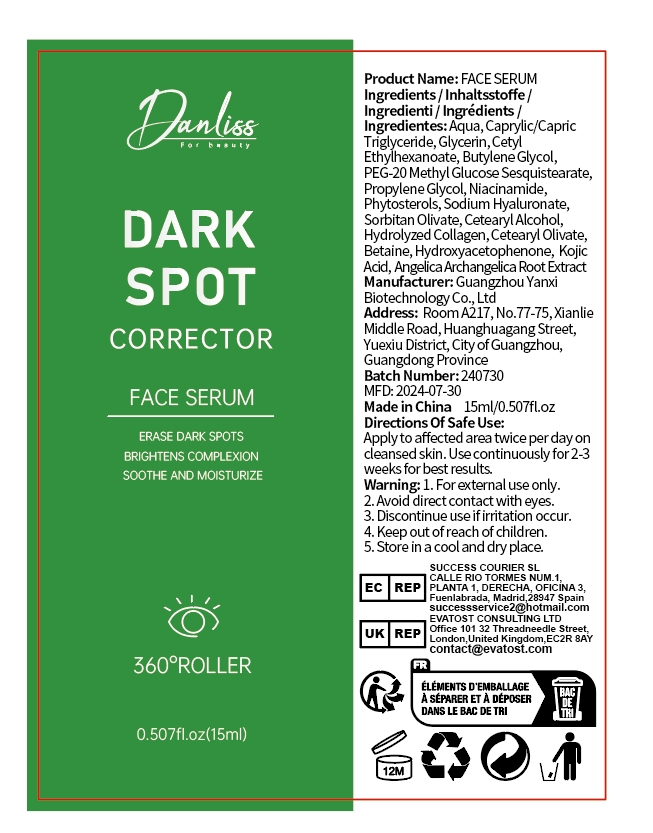 DRUG LABEL: FACE SERUM
NDC: 84025-206 | Form: CREAM
Manufacturer: Guangzhou Yanxi Biotechnology Co., Ltd
Category: otc | Type: HUMAN OTC DRUG LABEL
Date: 20241010

ACTIVE INGREDIENTS: CETYL ETHYLHEXANOATE 3 mg/100 mL; GLYCERIN 5 mg/100 mL
INACTIVE INGREDIENTS: WATER

DOSAGE AND ADMINISTRATION

use as face cream

WARNINGS

keep out of children

INACTIVE INGREDIENT

Aqua

INDICATIONS AND USAGE

for daily face care

keep out of children

PURPOSE

Moisturize the face